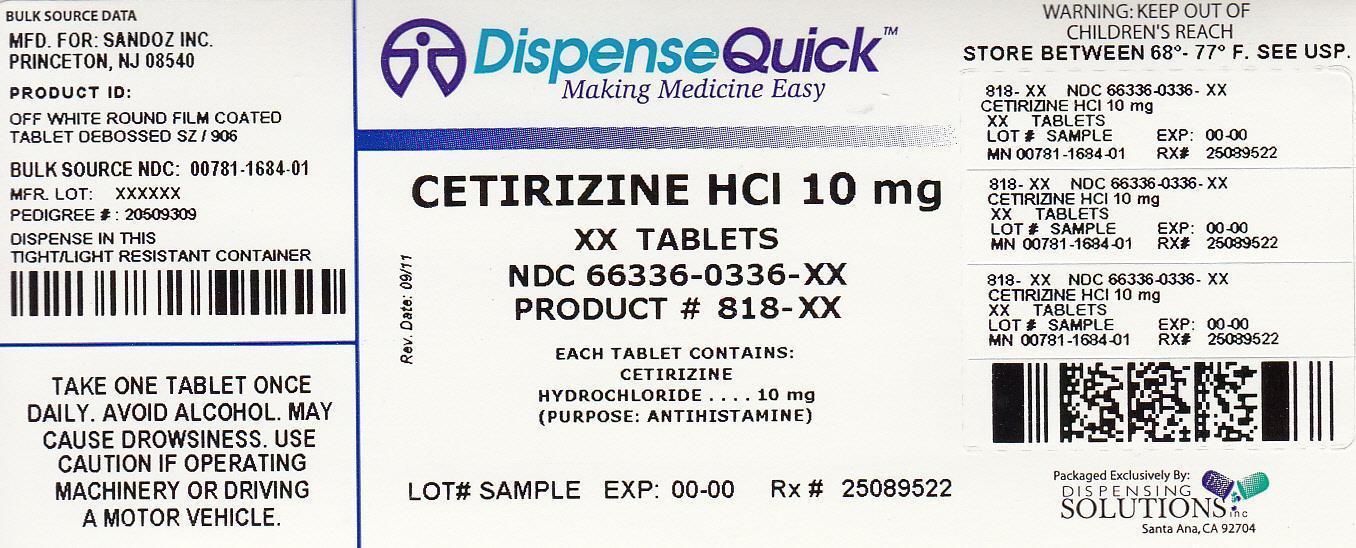 DRUG LABEL: Cetirizine Hydrochloride
NDC: 66336-336 | Form: TABLET
Manufacturer: Dispensing Solutions, Inc.
Category: otc | Type: HUMAN OTC DRUG LABEL
Date: 20120927

ACTIVE INGREDIENTS: CETIRIZINE HYDROCHLORIDE 10 mg/1 1
INACTIVE INGREDIENTS: STARCH, CORN; HYPROMELLOSES; LACTOSE MONOHYDRATE; MAGNESIUM STEARATE; POVIDONE; TITANIUM DIOXIDE; POLYETHYLENE GLYCOLs

Drug Facts

Active ingredient

(in each tablet)

Cetirizine HCl 10 mg

Purpose

Antihistamine

Uses

Temporarily relieves these symptoms due to hay fever or other upper respiratory allergies:

- runny nose
- sneezing
- itchy, watery eyes
- itching of the nose or throat

Warnings

Do not use if you have ever had an allergic reactions to this product or any of its ingredients or to an antihistamine containing hydroxyzine.

Ask a doctor before use if you have liver or kidney disease. Your doctor should determine if you need a different dose.

Ask a doctor or pharmacist before use if you are taking tranquilizers or sedatives.

When using this product

- drowsiness may occur
- avoid alcoholic drinks
- alcohol, sedatives, and tranquilizers may increase drowsiness
- be careful when driving a motor vehicle or operating machinery

Stop use and ask a doctor if an allergic reaction to this product occurs. Seek medical help right away.

If pregnant or breast-feeding:

- if breast-feeding: not recommended
- if pregnant: ask a health professional before use.

Keep out of reach of children. In case of overdose, get medical help or contact a Poison Control Center right away.

Keep out of reach of children. In case of overdose, get medical help or contact a Poison Control Center right away.

Directions

adults and children 6 years and over | One 10 mg tablet once daily; do not take more than one 10 mg tablet in 24 hours. A 5 mg product may be appropriate for less severe symptoms.
adults 65 years and over | ask a doctor
children under 6 years of age | ask a doctor
consumers with liver or kidney disease | ask a doctor

Other information

- Store between 20 to 25 C (68 to 77 F)

Inactive ingredients

Corn starch, hypromellose, lactose monohydrate, macrogol, magnesium stearate, povidone and titanium dioxide.

Questions? 1-800-525-8747

Manufactured in India by Sandoz Private Ltd.,

Principal Display Panel

NDC 66336-0336-XX

NDC 66336-0336-14

Cetirizine HCl Tablets
10 mg
antihistamine
Tablets.
ALLERGY
Indoor and Outdoor Allergies
24 hour Relief of
* Sneezing
* Runny Nose
* Itchy, Watery Eyes
* Itchy Throat or Nose